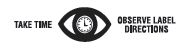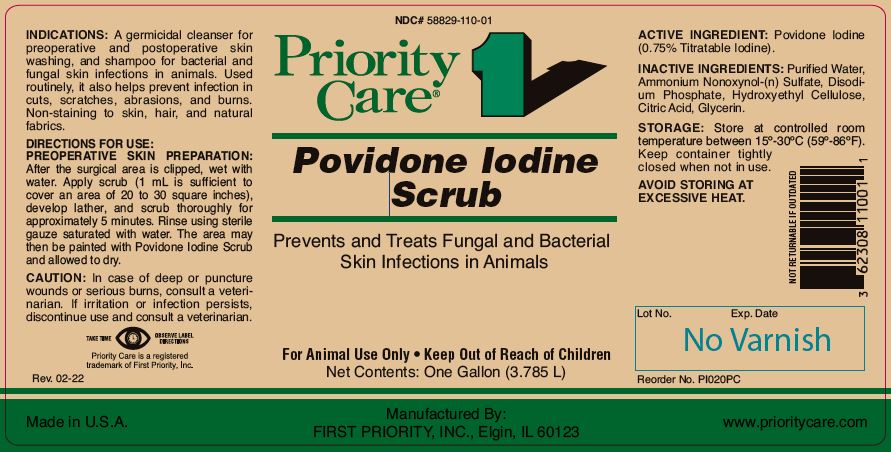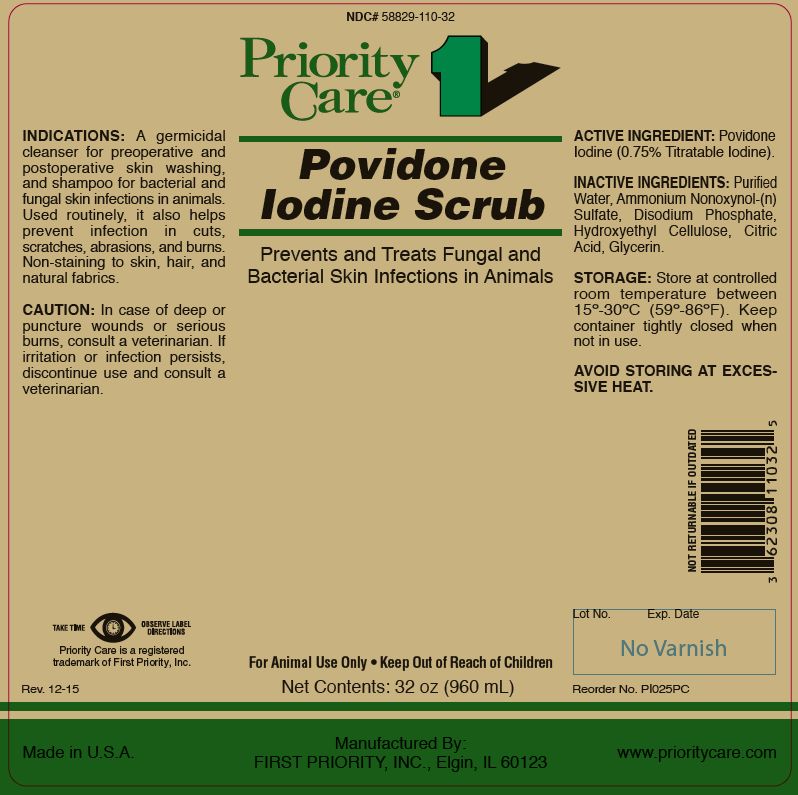 DRUG LABEL: POVIDONE IODINE SCRUB
NDC: 58829-110 | Form: LIQUID
Manufacturer: FIRST PRIORITY INCORPORATED
Category: animal | Type: OTC ANIMAL DRUG LABEL
Date: 20240307

ACTIVE INGREDIENTS: POVIDONE-IODINE 5.1 g/1 L

Povidone Iodine Scrub

PURPOSE

Prevents and Treats Fungal and Bacterial Skin Infections in Animals

KEEP OUT OF REACH OF CHILDREN

For Animal Use Only • Keep Out of Reach of Children

INDICATIONS:

A germicidal cleanser for preoperative and postoperative skin washing, and shampoo for bacterial and fungal skin infections in animals. Used routinely, it also helps prevent infection in cuts, scratches, abrasions, and burns. Non-staining to skin, hair, and natural fabrics.

DIRECTIONS FOR USE: PREOPERATIVE SKIN PREPARATION:

After the surgical area is clipped, wet with water. Apply scrub (1 mL is sufficient to cover an area of 20 to 30 square inches), develop lather, and scrub thoroughly for approximately 5 minutes. Rinse using sterile gauze saturated with water. The area may then be painted with Povidone Iodine Scrub and allowed to dry.

CAUTION:

In case of deep or puncture wounds or serious burns, consult a veterinarian. If irritation or infection persists, discontinue use and consult a veterinarian.

ACTIVE INGREDIENT:

Povidone Iodine (0.75% Titratable Iodine).

INACTIVE INGREDIENTS:

Purified Water, Ammonium Nonoxynol-(n) Sulfate, Disodium Phosphate, Hydroxyethyl Cellulose, Citric Acid, Glycerin.

STORAGE:

Store at controlled room temperature between 15º-30ºC (59º-86ºF). Keep container tightly closed when not in use.

AVOID STORING AT EXCESSIVE HEAT.

Net Contents:

32 oz (960 mL) Reorder No. PI025PC

One Gallon (3.785 L) Reorder No. PI020PC

INFORMATION FOR OWNERS/CAREGIVERS

Priority Care is a registered trademark of First Priority, Inc.

Made in U.S.A.

Manufactured By: FIRST PRIORITY, INC., Elgin, IL 60123

www.prioritycare.com

NOT RETURNABLE IF OUTDATED